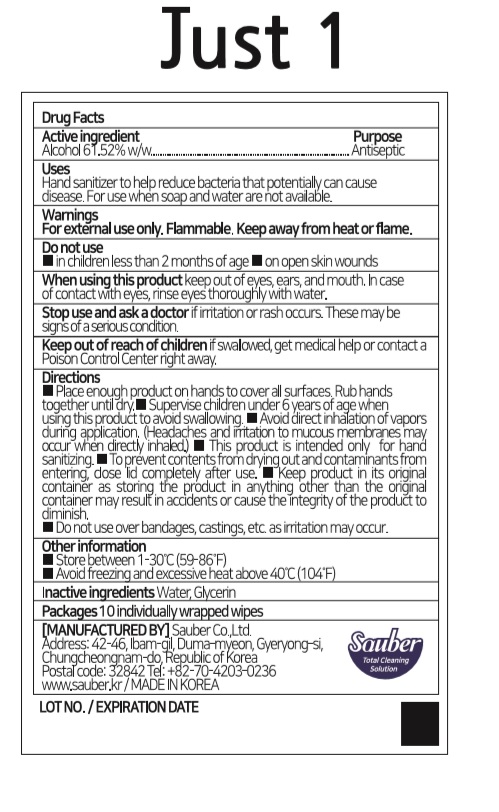 DRUG LABEL: Just 1
NDC: 78880-062 | Form: CLOTH
Manufacturer: Sauber Co.,Ltd.
Category: otc | Type: HUMAN OTC DRUG LABEL
Date: 20200710

ACTIVE INGREDIENTS: ALCOHOL 0.6152 1/1 1
INACTIVE INGREDIENTS: GLYCERIN; WATER

Just 1 | 10 ct. in 1 BOX | 78880-062-10 | HAND SANITIZING WIPES